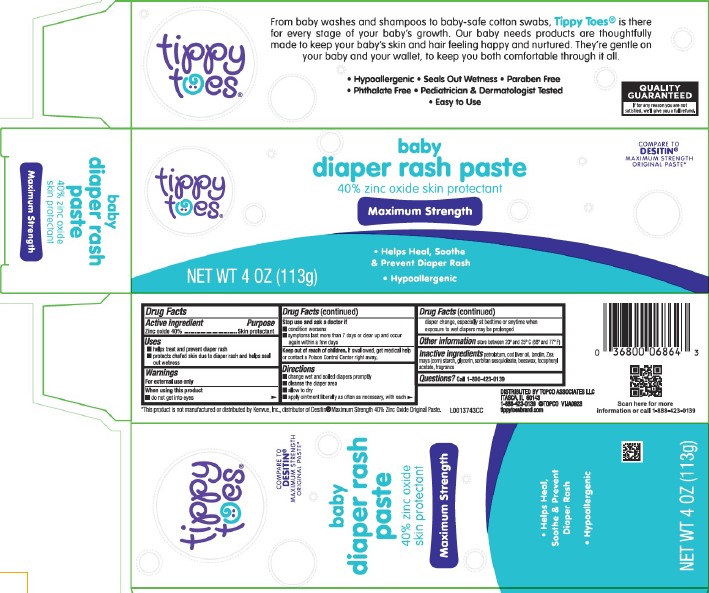 DRUG LABEL: Diaper Rash
NDC: 36800-020 | Form: PASTE
Manufacturer: Topco Associates LLC
Category: otc | Type: HUMAN OTC DRUG LABEL
Date: 20260213

ACTIVE INGREDIENTS: ZINC OXIDE 400 mg/1 g
INACTIVE INGREDIENTS: PETROLATUM; COD LIVER OIL; LANOLIN; STARCH, CORN; GLYCERIN; SORBITAN SESQUIOLEATE; YELLOW WAX; .ALPHA.-TOCOPHEROL ACETATE

Tippy Toes 020.002/020AC-AD
Diaper Rash Ointment 40% Zinc Oxide

Active Ingredient

Zinc oxide 40%

Purpose

Skin protectant

Uses

- helps treat and prevent diaper rash
- protects chafed skin due to diaper rash and helps seal out wetness

Warnings

For external use only

When using this product

- do not get into eyes

Stop use and ask a doctor if

- condition worsens
- symptoms last more than 7 days or clear up and occur again within a few days

Keep out of reach of children.

If swallowed, get medical help or contact a Poison Control Center right away.

Directions

- change wet and soilded diapers promptly
- cleanse the diaper area
- allow to dry
- apply ointment liberally as often as necessary, with each diaper change, especially at bedtime or anytime when exposure to wet diapers may be prolonged

Other information

store between 20⁰ and 25⁰C (68⁰ and 77⁰F)

Inactive ingredients

petrolatum, cod liver oil, lanolin, Zea mays (corn) starch, glycerin, sorbitan sesquioleate, beeswax, tocopheryl acetate, fragrance

Questions?

Call 1-800-423-0139

Claims

From baby washes and shampoos to baby-safe cotton swabs, Tippy Toes® is there for every single stage of your baby's growth. Our baby needs products are thoughtfully made to keep your baby's skin and hair feeling happy and nurtured. They're gentle on your baby and your wallet, to keep you both comfortable through it all.

- Hypoallergenic
- Seals out wetness
- Paraben Free
- Phthalate Free
- Pediatrician & Dermatologist Tested
- Easy to use

Disclaimer

*This product is not manufactured or distributed by Kenvue, Inc., distributor of Desitin®Maximum Strength 40% Zinc Oxide Original Paste.

Adverse reaction

DISTRIBUTED BY TOPCO ASSOCIATES LLC,

ITASCA, IL 60143

1-888-423-0139 ©TOPCO VIJA0923

tippytoesbytopcare.com

Scan here for more information or call 1-888-423-0139

QUALITY GUARANTEED

If for any reason you are not satisfied, we'll give you a full refund.

Principal display panel

tippy toes®

COMPARE TO DESITIN® MAXIMUM STRENGTH ORIGINAL PASTE*

baby diaper rash paste

40% zinc oxide

skin protectant

Maximum Strength

- helps heal, soothe & prevent diaper rash
- hypoallergenic

NET WT 4 OZ (113 g)